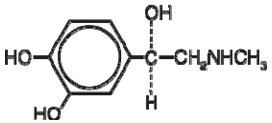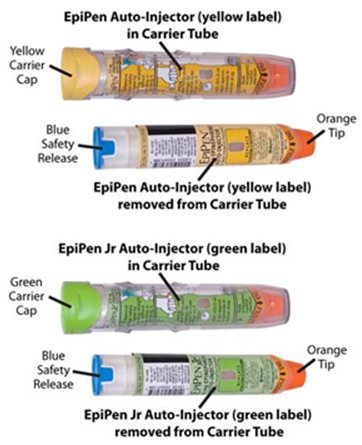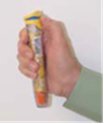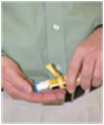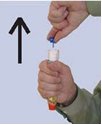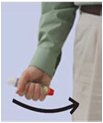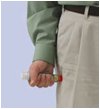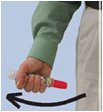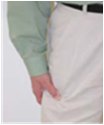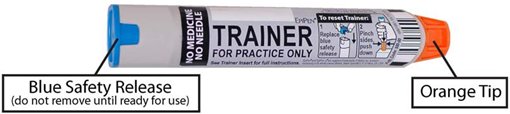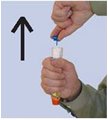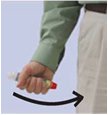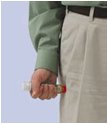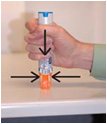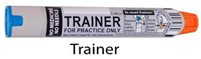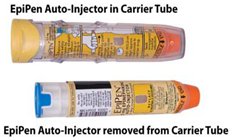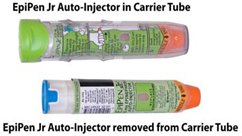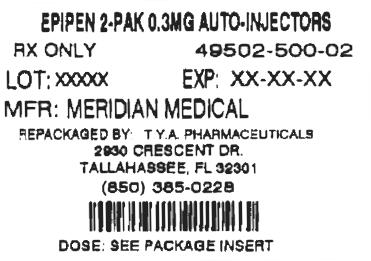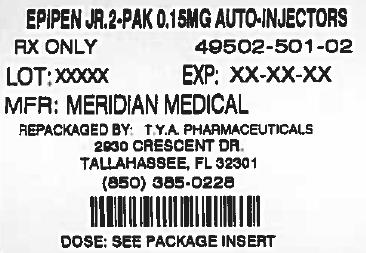 DRUG LABEL: EPIPEN
NDC: 64725-0500 | Form: INJECTION
Manufacturer: TYA Pharmaceuticals
Category: prescription | Type: HUMAN PRESCRIPTION DRUG LABEL
Date: 20140501

ACTIVE INGREDIENTS: EPINEPHRINE 0.3 mg/0.3 mL
INACTIVE INGREDIENTS: SODIUM CHLORIDE; SODIUM METABISULFITE; HYDROCHLORIC ACID

HIGHLIGHTS OF PRESCRIBING INFORMATION

These highlights do not include all the information needed to use safely and effectively. See full prescribing information for . Initial U.S. Approval: 1939 EPIPEN and EPIPEN Jr®® EPIPEN and EPIPEN Jr
EPIPEN (epinephrine injection), Auto-Injector 0.3 mg, EPIPEN Jr (epinephrine injection) Auto-Injector 0.15 mg, for intramuscular or subcutaneous use®®

1 INDICATIONS AND USAGE

EpiPen and EpiPen Jr contain epinephrine, a non-selective alpha and beta-adrenergic receptor agonist, indicated in the emergency treatment of allergic reactions (Type I) including anaphylaxis. () 1

2 DOSAGE AND ADMINISTRATION

- Patients greater than or equal to 30 kg (66 lbs): EpiPen 0.3 mg () 2
- Patients 15 to 30 kg (33 lbs to 66 lbs): EpiPen Jr 0.15 mg () 2

Inject EpiPen and EpiPen Jr intramuscularly or subcutaneously into the anterolateral aspect of the thigh, through clothing if necessary. Each device is a single-use injection () .2

3 DOSAGE FORMS AND STRENGTHS

- EpiPen: Injection, 0.3 mg: 0.3 mg/0.3 mL epinephrine, USP, pre-filled auto-injector () 3
- EpiPen Jr: Injection, 0.15 mg: 0.15 mg/0.3 mL epinephrine, USP, pre-filled auto-injector () 3

4 CONTRAINDICATIONS

None () 4

5 WARNINGS AND PRECAUTIONS

- In conjunction with use, seek immediate medical or hospital care. () 5.1
- Do not inject intravenously, into buttock, or into digits, hands, or feet. () 5.2
- The presence of a sulfite in this product should not deter use. () 5.3
- Administer with caution in patients with heart disease; may aggravate angina pectoris or produce ventricular arrhythmias. () 5.4

6 ADVERSE REACTIONS

Adverse reactions to epinephrine include anxiety, apprehensiveness, restlessness, tremor, weakness, dizziness, sweating, palpitations, pallor, nausea and vomiting, headache, and/or respiratory difficulties. () 6

To report SUSPECTED ADVERSE REACTIONS, contact Mylan Specialty, L.P. at 1-877-446-3679 (1-877-4-INFO-RX) or FDA at 1-800-FDA-1088 orwww.fda.gov/medwatch.

7 DRUG INTERACTIONS

- Cardiac glycosides or diuretics: observe for development of cardiac arrhythmias. () 7
- Tricyclic antidepressants, monoamine oxidase inhibitors, levothyroxine sodium, and certain antihistamines: potentiate effects of epinephrine. () 7
- Beta-adrenergic blocking drugs: antagonize cardiostimulating and bronchodilating effects of epinephrine. () 7
- Alpha-adrenergic blocking drugs: antagonize vasoconstricting and hypertensive effects of epinephrine. () 7
- Ergot alkaloids: may reverse the pressor effects of epinephrine. () 7

8 USE IN SPECIFIC POPULATIONS

- Elderly patients may be at greater risk of developing adverse reactions. (,) 5.48.5

FULL PRESCRIBING INFORMATION

1 INDICATIONS AND USAGE

EpiPen and EpiPen Jr are indicated in the emergency treatment of allergic reactions (Type I) including anaphylaxis to stinging insects (e.g., order Hymenoptera, which include bees, wasps, hornets, yellow jackets and fire ants) and biting insects (e.g., triatoma, mosquitoes), allergen immunotherapy, foods, drugs, diagnostic testing substances (e.g., radiocontrast media) and other allergens, as well as idiopathic anaphylaxis or exercise-induced anaphylaxis.

EpiPen and EpiPen Jr are intended for immediate administration in patients who are determined to be at increased risk for anaphylaxis, including individuals with a history of anaphylactic reactions.

Anaphylactic reactions may occur within minutes after exposure and consist of flushing, apprehension, syncope, tachycardia, thready or unobtainable pulse associated with a fall in blood pressure, convulsions, vomiting, diarrhea and abdominal cramps, involuntary voiding, wheezing, dyspnea due to laryngeal spasm, pruritus, rashes, urticaria or angioedema.

EpiPen and EpiPen Jr are intended for immediate administration as emergency supportive therapy only and are not a substitute for immediate medical care.

2 DOSAGE AND ADMINISTRATION

Selection of the appropriate dosage strength (EpiPen 0.3 mg or EpiPen Jr 0.15 mg) is determined according to patient body weight.

- Patients greater than or equal to 30 kg (approximately 66 pounds or more): EpiPen 0.3 mg
- Patients 15 to 30 kg (33 pounds to 66 pounds): EpiPen Jr 0.15 mg

Inject EpiPen or EpiPen Jr intramuscularly or subcutaneously into the anterolateral aspect of the thigh, through clothing if necessary.

Each EpiPen or EpiPen Jr contains a single dose of epinephrine for single-use injection. Since the doses of epinephrine delivered from EpiPen or EpiPen Jr are fixed, consider using other forms of injectable epinephrine if doses lower than 0.15 mg are deemed necessary.

The prescriber should carefully assess each patient to determine the most appropriate dose of epinephrine, recognizing the life-threatening nature of the reactions for which this drug is indicated. With severe persistent anaphylaxis, repeat injections with an additional EpiPen or EpiPen Jr may be necessary. More than two sequential doses of epinephrine should only be administered under direct medical supervision [ ]. see Warnings and Precautions (5.1)

The epinephrine solution in the clear window of the EpiPen Auto-Injector should be inspected visually for particulate matter and discoloration. Epinephrine is light sensitive and should be stored in the carrier tube provided to protect it from light [ ] see How Supplied/Storage and Handling (16.2).

3 DOSAGE FORMS AND STRENGTHS

- EpiPen: Injection, 0.3 mg/0.3 mL (0.3 mL, 1:1000) epinephrine injection, USP, pre-filled auto-injector
- EpiPen Jr: Injection, 0.15 mg/0.3 mL, (0.3 mL 1:2000) epinephrine injection, USP, pre-filled auto-injector

4 CONTRAINDICATIONS

None

5 WARNINGS AND PRECAUTIONS

5.1 Emergency Treatment

EpiPen and EpiPen Jr are intended for immediate administration as emergency supportive therapy and are not intended as a substitute for immediate medical care. More than two sequential doses of epinephrine should only be administered under direct medical supervision [ ]. In conjunction with the administration of epinephrine, the patient should seek immediate medical or hospital care. see , and Indications and Usage (1) Dosage and Administration (2) Patient Counseling Information (17)

5.2 Incorrect Locations of Injection

EpiPen and EpiPen Jr should be injected into the anterolateral aspect of the thigh [ ]. onlysee and Dosage and Administration (2) Patient Counseling Information (17)

- Large doses or accidental intravenous injection of epinephrine may result in cerebral hemorrhage due to sharp rise in blood pressure. Rapidly acting vasodilators can counteract the marked pressor effects of epinephrine if there is such inadvertent administration. Do not inject intravenously.
- Injection into the buttock may not provide effective treatment of anaphylaxis. Advise the patient to go immediately to the nearest emergency room for further treatment of anaphylaxis. Additionally, injection into the buttock has been associated with gas gangrene. Cleansing with alcohol does not kill bacterial spores, and therefore, does not lower this risk. Do not inject into buttock.
- Since epinephrine is a strong vasoconstrictor, accidental injection into the digits, hands or feet may result in loss of blood flow to the affected area. Advise the patient to go immediately to the nearest emergency room and to inform the healthcare provider in the emergency room of the location of the accidental injection. Treatment of such inadvertent administration should consist of vasodilation, in addition to further appropriate treatment of anaphylaxis [ ]. Do not inject into digits, hands or feet. see Adverse Reactions (6)

5.3 Allergic Reactions Associated With Sulfite

The presence of a sulfite in this product should not deter administration of the drug for treatment of serious allergic or other emergency situations even if the patient is sulfite-sensitive.

Epinephrine is the preferred treatment for serious allergic reactions or other emergency situations even though this product contains sodium metabisulfite, a sulfite that may, in other products, cause allergic-type reactions including anaphylactic symptoms or life-threatening or less severe asthmatic episodes in certain susceptible persons.

The alternatives to using epinephrine in a life-threatening situation may not be satisfactory.

5.4 Disease Interactions

Some patients may be at greater risk for developing adverse reactions after epinephrine administration. Despite these concerns, it should be recognized that the presence of these conditions is not a contraindication to epinephrine administration in an acute, life-threatening situation. Therefore, patients with these conditions, and/or any other person who might be in a position to administer EpiPen or EpiPen Jr to a patient experiencing anaphylaxis should be carefully instructed in regard to the circumstances under which epinephrine should be used.

- Patients with Heart Disease

Epinephrine should be administered with caution to patients who have heart disease, including patients with cardiac arrhythmias, coronary artery or organic heart disease, or hypertension In such patients, or in patients who are on drugs that may sensitize the heart to arrhythmias epinephrine may precipitate or aggravate angina pectoris as well as produce ventricular arrhythmias [ ]. ., see and Drug Interactions (7) Adverse Reactions (6)

- Other Patients and Diseases

Epinephrine should be administered with caution to patients with hyperthyroidism, diabetes, elderly individuals, and pregnant women. Patients with Parkinson’s disease may notice a temporary worsening of symptoms.

6 ADVERSE REACTIONS

Due to the lack of randomized, controlled clinical trials of epinephrine for the treatment of anaphylaxis, the true incidence of adverse reactions associated with the systemic use of epinephrine is difficult to determine. Adverse reactions reported in observational trials, case reports, and studies are listed below.

Common adverse reactions to systemically administered epinephrine include anxiety; apprehensiveness; restlessness; tremor; weakness; dizziness; sweating; palpitations; pallor; nausea and vomiting; headache; and/or respiratory difficulties. These symptoms occur in some persons receiving therapeutic doses of epinephrine, but are more likely to occur in patients with hypertension or hyperthyroidism [ ]. see Warnings and Precautions (5.4)

Arrhythmias, including fatal ventricular fibrillation, have been reported, particularly in patients with underlying cardiac disease or those receiving certain drugs [ ]. see and Warnings and Precautions (5.4) Drug Interactions (7)

Rapid rises in blood pressure have produced cerebral hemorrhage, particularly in elderly patients with cardiovascular disease [ ]. see Warnings and Precautions (5.4)

Angina may occur in patients with coronary artery disease [ ]. see Warnings and Precautions (5.4)

Accidental injection into the digits, hands or feet may result in loss of blood flow to the affected area [ ]. see Warnings and Precautions (5.2)

Adverse events experienced as a result of accidental injections may include increased heart rate, local reactions including injection site pallor, coldness and hypoesthesia or injury at the injection site resulting in bruising, bleeding, discoloration, erythema or skeletal injury.

Injection into the buttock has resulted in cases of gas gangrene [ ] see Warnings and Precautions (5.4).

7 DRUG INTERACTIONS

Patients who receive epinephrine while concomitantly taking cardiac glycosides, diuretics, or anti-arrhythmics should be observed carefully for the development of cardiac arrhythmias [ ]. see Warnings and Precautions (5.4)

The effects of epinephrine may be potentiated by tricyclic antidepressants, monoamine oxidase inhibitors, levothyroxine sodium, and certain antihistamines, notably chlorpheniramine, tripelennamine, and diphenhydramine.

The cardiostimulating and bronchodilating effects of epinephrine are antagonized by beta- adrenergic blocking drugs, such as propranolol.

The vasoconstricting and hypertensive effects of epinephrine are antagonized by alpha- adrenergic blocking drugs, such as phentolamine.

Ergot alkaloids may also reverse the pressor effects of epinephrine.

8 USE IN SPECIFIC POPULATIONS

8.1 Pregnancy

Teratogenic Effects Pregnancy Category C. .

There are no adequate and well controlled studies of the acute effect of epinephrine in pregnant women.

Epinephrine was teratogenic in rabbits, mice and hamsters. Epinephrine should be used during pregnancy only if the potential benefit justifies the potential risk to the fetus (fetal anoxia, spontaneous abortion, or both).

Epinephrine has been shown to have teratogenic effects when administered subcutaneously in rabbits at approximately 30 times the maximum recommended daily subcutaneous or intramuscular dose (on a mg/m basis at a maternal dose of 1.2 mg/kg/day for two to three days), in mice at approximately 7 times the maximum daily subcutaneous or intramuscular dose (on a mg/m basis at a maternal subcutaneous dose of 1 mg/kg/day for 10 days), and in hamsters at approximately 5 times the maximum recommended daily subcutaneous or intramuscular dose (on a mg/m basis at a maternal subcutaneous dose of 0.5 mg/kg/day for 4 days).^2^2^2

These effects were not seen in mice at approximately 3 times the maximum recommended daily subcutaneous or intramuscular dose (on a mg/m basis at a subcutaneous maternal dose of 0.5 mg/kg/day for 10 days).^2

8.3 Nursing Mothers

It is not known whether epinephrine is excreted in human milk. Because many drugs are excreted in human milk, caution should be exercised when EpiPen is administered to a nursing woman.

8.4 Pediatric Use

EpiPen or EpiPen Jr may be administered to pediatric patients at a dosage appropriate to body weight [ ] Clinical experience with the use of epinephrine suggests that the adverse reactions seen in children are similar in nature and extent to those both expected and reported in adults. Since the doses of epinephrine delivered from EpiPen and EpiPen Jr are fixed, consider using other forms of injectable epinephrine if doses lower than 0.15 mg are deemed necessary. see Dosage and Administration (2).

8.5 Geriatric Use

Clinical studies for the treatment of anaphylaxis have not been performed in subjects aged 65 and over to determine whether they respond differently from younger subjects. However, other reported clinical experience with use of epinephrine for the treatment of anaphylaxis has identified that geriatric patients may be particularly sensitive to the effects of epinephrine. Therefore, EpiPen should be administered with caution in elderly individuals, who may be at greater risk for developing adverse reactions after epinephrine administration [ ]. see , Warnings and Precautions (5.4) Overdosage (10)

10 OVERDOSAGE

Overdosage of epinephrine may produce extremely elevated arterial pressure, which may result in cerebrovascular hemorrhage, particularly in elderly patients. Overdosage may also result in pulmonary edema because of peripheral vascular constriction together with cardiac stimulation. Treatment consists of rapidly acting vasodilators or alpha-adrenergic blocking drugs and/or respiratory support.

Epinephrine overdosage can also cause transient bradycardia followed by tachycardia, and these may be accompanied by potentially fatal cardiac arrhythmias. Premature ventricular contractions may appear within one minute after injection and may be followed by multifocal ventricular tachycardia (prefibrillation rhythm). Subsidence of the ventricular effects may be followed by atrial tachycardia and occasionally by atrioventricular block. Treatment of arrhythmias consists of administration of a beta-adrenergic blocking drug such as propranolol.

Overdosage sometimes results in extreme pallor and coldness of the skin, metabolic acidosis, and kidney failure. Suitable corrective measures must be taken in such situations.

11 DESCRIPTION

EpiPen (epinephrine injection, USP) 0.3 mg and EpiPen Jr (epinephrine injection, USP) 0.15 mg are auto-injectors and combination products containing drug and device components.

Each EpiPen Auto-Injector, 0.3 mg delivers a single dose of 0.3 mg epinephrine from epinephrine injection, USP 1:1000 (0.3 mL) in a sterile solution.

Each EpiPen Jr Auto-Injector, 0.15 mg delivers a single dose of 0.15 mg epinephrine from epinephrine injection, USP 1:2000 (0.3 mL) in a sterile solution.

The EpiPen and EpiPen Jr each contain 2 mL epinephrine solution. Approximately 1.7 mL remains in the auto-injector after activation, but is not available for future use, and should be discarded.

Each 0.3 mL in the EpiPen Auto-Injector contains 0.3 mg epinephrine, 1.8 mg sodium chloride, 0.5 mg sodium metabisulfite, hydrochloric acid to adjust pH, and Water for Injection. The pH range is 2.2–5.0.

Each 0.3 mL in the EpiPen Jr Auto-Injector contains 0.15 mg epinephrine, 1.8 mg sodium chloride, 0.5 mg sodium metabisulfite, hydrochloric acid to adjust pH, and Water for Injection. The pH range is 2.2-5.0.

Epinephrine is a sympathomimetic catecholamine. Chemically, epinephrine is (-)-3,4- Dihydroxy-α-[(methylamino)methyl]benzyl alcohol with the following structure:

Epinephrine solution deteriorates rapidly on exposure to air or light, turning pink from oxidation to adrenochrome and brown from the formation of melanin. Replace EpiPen and EpiPen Jr if the epinephrine solution appears discolored (pinkish or brown color), cloudy, or contains particles.

Thoroughly review the patient instructions and operation of EpiPen or EpiPen Jr with patients and caregivers prior to use. [ ]. see Patient Counseling Information (17)

12 CLINICAL PHARMACOLOGY

12.1 Mechanism of Action

Epinephrine acts on both alpha- and beta-adrenergic receptors.

12.2 Pharmacodynamics

Through its action on alpha-adrenergic receptors, epinephrine lessens the vasodilation and increased vascular permeability that occurs during anaphylaxis, which can lead to loss of intravascular fluid volume and hypotension.

Through its action on beta-adrenergic receptors, epinephrine causes bronchial smooth muscle relaxation and helps alleviate bronchospasm, wheezing and dyspnea that may occur during anaphylaxis.

Epinephrine also alleviates pruritus, urticaria, and angioedema and may relieve gastrointestinal and genitourinary symptoms associated with anaphylaxis because of its relaxer effects on the smooth muscle of the stomach, intestine, uterus and urinary bladder.

When given subcutaneously or intramuscularly, epinephrine has a rapid onset and short duration of action.

13 NONCLINICAL TOXICOLOGY

13.1 Carcinogenesis, Mutagenesis, Impairment of Fertility

Long-term studies to evaluate the carcinogenic potential of epinephrine have not been conducted.

Epinephrine and other catecholamines have been shown to have mutagenic potential and to be an oxidative mutagen in a bacterial reverse mutation assay. in vitro WP2

Epinephrine was positive in the DNA Repair test with (REC) assay, but was not mutagenic in the bacterial reverse mutation assay. B. subtilis Salmonella

The potential for epinephrine to impair fertility has not been evaluated.

This should not prevent the use of epinephrine under the conditions noted under . Indications and Usage (1)

16 HOW SUPPLIED/STORAGE AND HANDLING

NDC:64725-0500-1 in a CARTON of 1 INJECTIONS

16.1 How Supplied

EpiPen Auto-Injectors (epinephrine injections, USP, 1:1000, 0.3 mL) are available as EpiPen 2-Pak , NDC 49502-500-02, a pack that contains two EpiPen Auto-Injectors (epinephrine injections, USP, 1:1000, 0.3 mL) and one EpiPen Auto-Injector trainer device.®

EpiPen Jr Auto-Injectors (epinephrine injections, USP, 1:2000, 0.3 mL) are available as EpiPen Jr 2-Pak , NDC 49502-501-02, a pack that contains two EpiPen Jr Auto-Injectors (epinephrine injections, USP, 1:2000, 0.3 mL) and one EpiPen Auto-Injector trainer device.®

EpiPen 2-Pak and EpiPen Jr 2-Pak also includes an S-clip to clip two carrier tubes together.®®

Rx only

16.2 Storage and Handling

Protect from light. Epinephrine is light sensitive and should be stored in the carrier tube provided to protect it from light. Store at 20° to 25°C (68° to 77°F); excursions permitted to 15° to 30°C (59° to 86°F) (See USP Controlled Room Temperature). Do not refrigerate. Before using, check to make sure the solution in the auto-injector is clear and colorless. Replace the auto-injector if the solution is discolored (pinkish or brown color), cloudy, or contains particles.

17 PATIENT COUNSELING INFORMATION

[ ] see FDA-Approved Patient Labeling () Patient Information and Instructions for Use

A healthcare provider should review the patient instructions and operation of EpiPen and EpiPen Jr in detail, with the patient or caregiver.

Epinephrine is essential for the treatment of anaphylaxis. Patients who are at risk of or with a history of severe allergic reactions (anaphylaxis) to insect stings or bites, foods, drugs, and other allergens, as well as idiopathic and exercise-induced anaphylaxis, should be carefully instructed about the circumstances under which epinephrine should be used.

Administration and Training

Patients and/or caregivers should be instructed in the appropriate use of EpiPen and EpiPen Jr. EpiPen should be injected into the middle of the outer thigh (through clothing, if necessary). Each device is a single-use injection. Advise patients to seek immediate medical care in conjunction with administration of EpiPen.

Complete patient information, including dosage, directions for proper administration and precautions can be found inside each EpiPen or EpiPen Jr carton. A printed label on the surface of EpiPen shows instructions for use and a diagram depicting the injection process.

Patients and/or caregivers should be instructed to use the Trainer to familiarize themselves with the use of EpiPen in an allergic emergency. The Trainer may be used multiple times. A Trainer device is provided in 2-Pak cartons.

Adverse Reactions

Epinephrine may produce symptoms and signs that include an increase in heart rate, the sensation of a more forceful heartbeat, palpitations, sweating, nausea and vomiting, difficulty breathing, pallor, dizziness, weakness or shakiness, headache, apprehension, nervousness, or anxiety. These signs and symptoms usually subside rapidly, especially with rest, quiet and recumbency. Patients with hypertension or hyperthyroidism may develop more severe or persistent effects, and patients with coronary artery disease could experience angina. Patients with diabetes may develop increased blood glucose levels following epinephrine administration. Patients with Parkinson’s disease may notice a temporary worsening of symptoms [ ] see Warnings and Precautions (5.4).

Accidental Injection

Advise patients to seek immediate medical care in the case of accidental injection. Since epinephrine is a strong vasoconstrictor when injected into the digits, hands, or feet, treatment should be directed at vasodilatation if there is such an accidental injection to these areas [ ]. see Warnings and Precautions (5.2)

Storage and Handling

Instruct patients to inspect the epinephrine solution visually through the clear window of the auto-injector periodically. EpiPen and EpiPen Jr should be replaced if the epinephrine solution appears discolored (pinkish or brown color), cloudy, or contains particles. Epinephrine is light sensitive and should be stored in the carrier tube provided to protect it from light. The carrier tube is not waterproof. Patients should be instructed that EpiPen and EpiPen Jr must be used or properly disposed once the blue safety release is removed or after use [ ]. see Storage and Handling (16.2)

Complete patient information, including dosage, directions for proper administration and precautions can be found inside each EpiPen Auto-Injector carton.

Manufactured for Mylan Specialty L.P., Morgantown, WV 26505, U.S.A. by Meridian Medical Technologies, Inc., Columbia, MD 21046, U.S.A., a Pfizer company

EpiPen and EpiPen Jr are registered trademarks of Mylan Inc. licensed exclusively to its wholly-owned affiliate, Mylan Specialty L. P. of Morgantown, WV 26505, U.S.A.®®

©2014 by Meridian Medical Technologies, Inc.

PATIENT INFORMATION and INSTRUCTIONS FOR USE

EPIPEN (epinephrine) Auto-Injector 0.3 mg Epipen = one dose of 0.30 mg epinephrine (USP, 1:1000, 0.3 mL) EPIPEN JR (epinephrine) Auto-Injector 0.15 mg Epipen Jr = one dose of 0.15 mg epinephrine (USP, 1:2000, 0.3 mL)®
®
®
®

For allergic emergencies (anaphylaxis)

Patient Information

Read this Patient Information Leaflet carefully before using the EpiPen or EpiPen Jr Auto-Injector and each time you get a refill. There may be new information. You, your parent, caregiver, or others who may be in a position to administer EpiPen or EpiPen Jr Auto-Injector, should know how to use it before you have an allergic emergency.®®

This information does not take the place of talking with your healthcare provider about your medical condition or your treatment.

What is the most important information I should know about the EpiPen and EpiPen Jr?

1. EpiPen and EpiPen Jr contain, a medicine used to treat allergic emergencies (anaphylaxis). Anaphylaxis can be life threatening, can happen with minutes, and can be caused by stinging and biting insects, allergy injections, foods, medicines, exercise, or unknown causes.
Symptoms of anaphylaxis may include:
  - trouble breathing
  - wheezing
  - hoarseness (changes in the way your voice sounds)
  - hives (raised reddened rash that may itch)
  - severe itching
  - swelling of your face, lips, mouth, or tongue
  - skin rash, redness, or swelling
  - fast heartbeat
  - weak pulse
  - feeling very anxious
  - confusion
  - stomach pain
  - losing control of urine or bowel movements (incontinence)
  - diarrhea or stomach cramps
  - dizziness, fainting, or “passing out” (unconsciousness)
2. Always carry your EpiPen or EpiPen Jr with you because you may not know when anaphylaxis may happen.
Talk to your healthcare provider if you need additional units to keep at work, school, or other locations. Tell your family members, caregivers, and others where you keep your EpiPen or EpiPen Jr and how to use it before you need it. You may be unable to speak in an allergic emergency.
3. When you have an allergic emergency (anaphylaxis)
  - Use EpiPen or EpiPen Jr right away.
  - You may need further medical attention. You may need to use a second EpiPen or EpiPen Jr if symptoms continue or recur. Only a healthcare provider should give additional doses of epinephrine if you need more than 2 injections for a single anaphylaxis episode. Get emergency medical help right away.

What are EpiPenand EpiPen Jr?

- EpiPen and EpiPen Jr are disposable, prefilled automatic injection devices (auto-injectors) used to treat life-threatening, allergic emergencies including anaphylaxis in people who are at risk for or have a history of serious allergic emergencies. Each device contains a single dose of epinephrine.
- EpiPen and EpiPen Jr are for immediate self (or caregiver) administration and do not take the place of emergency medical care. You should get emergency help right away after using EpiPen and EpiPen Jr.
- EpiPen and EpiPen Jr are for people who have been prescribed this medicine by their healthcare provider.
- The EpiPen Auto-Injector (0.3 mg) is for patients who weigh 66 pounds or more (30 kilograms or more).
- The EpiPen Jr Auto-Injector (0.15 mg) is for patients who weigh about 33 to 66 pounds (15 to 30 kilograms).
- It is not known if EpiPen and EpiPen Jr are safe and effective in children who weigh less than 33 pounds (15 kilograms).

What should I tell my healthcare provider before using the EpiPen or EpiPen Jr?

Before you use EpiPen or EpiPen Jr, tell your healthcare providerabout all your medical conditions, but especially if you:

- have heart problems or high blood pressure
- have diabetes
- have thyroid problems
- have asthma
- have a history of depression
- have Parkinson’s disease
- have any other medical conditions
- are pregnant or plan to become pregnant. It is not known if epinephrine will harm your unborn baby.
- are breastfeeding or plan to breastfeed. It is not known if epinephrine passes into your breast milk.

, including prescription and over-the-counter medicines, vitamins, and herbal supplements. Tell your healthcare provider of all known allergies. Tell your healthcare provider about all the medicines you take

Especially tell your healthcare provider if you take certain asthma medicines.

EpiPen or EpiPen Jr and other medicines may affect each other, causing side effects. EpiPen or EpiPen Jr may affect the way other medicines work, and other medicines may affect how EpiPen or EpiPen Jr works.

Know the medicines you take. Keep a list of them to show your healthcare provider and pharmacist when you get a new medicine.

Use your EpiPen or EpiPen Jr for treatment of anaphylaxis as prescribed by your healthcare provider, regardless of your medical conditions or the medicines you take.

How should I use EpiPen and EpiPen Jr?

- Each EpiPen or EpiPen Jr Auto-Injector contains only 1 dose of medicine.
- EpiPen or EpiPen Jr should be injected into the middle of your outer thigh (upper leg). It can be injected through your clothing if needed.
- Read the Instructions for Use at the end of this Patient Information Leaflet about the right way to use EpiPen and EpiPen Jr.
- Your healthcare provider will show you how to safely use the EpiPen or EpiPen Jr Auto-Injector.
- Use your EpiPen or EpiPen Jr exactly as your healthcare provider tells you to use it. You may need to use a second EpiPen or EpiPen Jr if symptoms continue or recur. Only a healthcare provider should give additional doses of epinephrine if you need more than 2 injections for a single anaphylaxis episode.
- The needle comes out of the orange tip. Accidental injection into finger, hands or feet may cause a loss of blood flow to these areas. Tell the healthcare provider where on your body you received the accidental injection. Caution: Never put your thumb, fingers, or hand over the orange tip. Never press or push the orange tip with your thumb, fingers, or hand. If this happens, go immediately to the nearest emergency room.
- Your EpiPen and EpiPen Jr Auto-Injector may come packaged with an EpiPen Trainer and separate Trainer Instructions for Use. Periodically practice with your EpiPen Trainer before an allergic emergency happens to make sure you are able to safely use the real EpiPen and EpiPen Jr Auto-Injector in an emergency. Always carry your real EpiPen or EpiPen Jr Auto-Injector with you in case of an allergic emergency. Additional training resources are available at www.epipen.com. The EpiPen Trainer has a grey color. The grey EpiPen Trainer contains no medicine and no needle.
- Do not drop the carrier tube or auto-injector. If the carrier tube or auto-injector is dropped, check for damage and leakage. Dispose of the auto-injector and carrier tube, and replace if damage or leakage is noticed or suspected.

What are the possible side effects of the EpiPen and EpiPen Jr?

EpiPen and EpiPen Jr may cause serious side effects.

- inject the EpiPen or EpiPen Jr into your: The EpiPen or EpiPen Jr should only be injected into the middle of your outer thigh (upper leg). Do not
  - veins
  - buttocks
  - fingers, toes, hands, or feet
If you accidentally inject EpiPen or EpiPen Jr into any other part of your body, go to the nearest emergency room right away. Tell the healthcare provider where on your body you received the accidental injection.
- Talk to your healthcare provider about all your medical conditions. If you have certain medical conditions, or take certain medicines, your condition may get worse or you may have longer lasting side effects when you use your EpiPen or EpiPen Jr.

Common side effects of EpiPen and EpiPen Jr include:

- fast, irregular or “pounding” heartbeat
- sweating
- headache
- weakness
- shakiness
- paleness
- feelings of over excitement, nervousness or anxiety
- dizziness
- nausea or vomiting
- breathing problems

These side effects may go away with rest. Tell your healthcare provider if you have any side effect that bothers you or that does not go away.

These are not all the possible side effects of the EpiPen or EpiPen Jr. For more information, ask your healthcare provider or pharmacist.

Call your healthcare provider for medical advice about side effects. You may report side effects to FDA at 1-800-FDA-1088.

How should I store EpiPen and EpiPen Jr?

- Store EpiPen and EpiPen Jr at room temperature between 68° to 77° F (20° to 25° C).
- Protect from light.
- expose to extreme cold or heat. For example, store in your vehicle’s glove box and store in the refrigerator or freezer. Do notdonotdonot
- Examine the contents in the clear window of your auto-injector periodically. The solution should be clear. If the solution is discolored (pinkish or brown color) or contains solid particles, replace the unit.
- Always keep your EpiPen or EpiPen Jr Auto-Injector in the carrier tube to protect it from damage; however, the carrier tube is not waterproof.
- The blue safety release helps to prevent accidental injection. Keep the blue safety release on until you need to use EpiPen or EpiPen Jr.
- Your EpiPen or EpiPen Jr has an expiration date. Replace it before the expiration date.

Keep EpiPen and EpiPen Jr and all medicines out of the reach of children.

General information about the safe and effective use of EpiPen and EpiPen Jr:

Medicines are sometimes prescribed for purposes other than those listed in a Patient Information Leaflet. Do not use the EpiPen or EpiPen Jr for a condition for which it was not prescribed. Do not give your EpiPen or EpiPen Jr to other people.

This Patient Information Leaflet summarizes the most important information about EpiPen and EpiPen Jr. If you would like more information, talk to your healthcare provider. You can ask your pharmacist or healthcare provider for information about EpiPen and EpiPen Jr that is written for health professionals.

For more information and video instructions on the use of EpiPen and EpiPen Jr, go to or call 1-800-395-3376. www.epipen.com

What are the ingredients in EpiPen and EpiPen Jr?

Epinephrine Active Ingredients:
sodium chloride, sodium metabisulfite, hydrochloric acid, and water. Inactive Ingredients:

Important Information

- The EpiPen Auto-Injector has a yellow colored label.
- The EpiPen Jr Auto-Injector has a green colored label.
- The EpiPen Trainer has a grey color and contains no medicine and no needle.
- Your auto-injector is designed to work through clothing.
- The blue safety release on the EpiPen and EpiPen Jr Auto-Injector helps to prevent accidental injection of the device. Do not remove the blue safety release until you are ready to use it.
- Only inject into the middle of the outer thigh (upper leg). Never inject into any other part of the body.
- Never put your thumb, fingers, or your hand over the orange tip. The needle comes out of the orange tip.
- If an accidental injection happens, get medical help right away.
- Do not place patient information or any other foreign objects in the carrier tube with the Auto-Injector, as this may prevent you from removing the Auto-Injector for use.

Instructions for Use

EPIPEN (epinephrine) Auto-Injector 0.3 mg Epipen = one dose of 0.30 mg epinephrine (USP, 1:1000, 0.3 mL) EPIPEN JR (epinephrine) Auto-Injector 0.15 mg Epipen Jr = one dose of 0.15 mg epinephrine (USP, 1:2000, 0.3 mL)®
®
®
®

For allergic emergencies (anaphylaxis)

Read these Instructions for Use carefully before you use EpiPen or EpiPen Jr. Before you need to use your EpiPen or EpiPen Jr, make sure your healthcare provider shows you the right way to use it. Parents, caregivers, and others who may be in a position to administer EpiPen or EpiPen Jr Auto-Injector should also understand how to use it as well. If you have any questions, ask your healthcare provider.

Your EpiPen and EpiPen Jr Auto-Injector

A dose of EpiPen or EpiPen Jr requires 3 simple steps: Prepare, Administer and Get emergency medical help®

Step 1. Prepare EpiPen or EpiPen Jr for injection

Remove the EpiPen or EpiPen Jr from the clear carrier tube.

Flip open the yellow cap of your EpiPen or the green cap of your EpiPen Jr carrier tube.

Tip and slide the auto-injector out of the carrier tube.

Grasp the auto-injector in your fist with the orange tip pointing downward.

With your other hand, without bending or twisting it remove the blue safety release by pulling straight up.

Note:
- The needle comes out of the orange tip.
- To avoid an accidental injection, never put your thumb, fingers or hand over the orange tip. If an accidental injection happens, get medical help right away

Step 2. Administer EpiPen or EpiPen Jr

Hold the auto-injector with orange tip near the middle of the outer thigh (upper leg). until it ‘clicks’. Keep the auto-injector firmly pushed against the thigh at a 90° angle (perpendicular) to the thigh. Swing and firmly push the orange tip against the middle of the outer thigh

to deliver the medicine. The injection is now complete. Hold firmly against the thigh for approximately 10 seconds

The orange tip will extend to cover the needle. Remove the auto-injector from the thigh.

Massage the injection area for 10 seconds.

You may need further medical attention. You may need to use a second EpiPen or EpiPen Jr Auto-Injector if symptoms continue or recur. Step 3. Get emergency medical help now.

- Take your used auto-injector with you when you go to see a healthcare provider.
- Tell the healthcare provider that you have received an injection of epinephrine. Show the healthcare provider where you received the injection.
- Give your used EpiPen or EpiPen Jr Auto-Injector to the healthcare provider for inspection and proper disposal.
- Ask for a refill, if needed.

Note:

- The used auto-injector with extended needle cover will not fit in the carrier tube.
- EpiPen and EpiPen Jr are single-use injectable devices that deliver a fixed dose of epinephrine. The auto-injector cannot be reused. It is normal for most of the medicine to remain in the auto-injector after the dose is injected. The correct dose has been administered if the orange needle tip is extended and the window is blocked.
- Your EpiPen and EpiPen Jr Auto-Injector may come packaged with an EpiPen Trainer and separate Trainer Instructions for Use. The EpiPen Trainer has a grey color. The grey EpiPen Trainer contains no medicine and no needle. Practice with your EpiPen Trainer, but always carry your real EpiPen or EpiPen Jr Auto-Injector in case of an allergic emergency.
- Do not try to take the EpiPen or EpiPen Jr Auto-Injector apart.

This Patient Information and Instructions for Use has been approved by the U.S. Food and Drug Administration.

Manufactured for:

Mylan Specialty L.P., Morgantown, WV 26505, U.S.A. by Meridian Medical Technologies, Inc., Columbia, MD 21046, U.S.A., a Pfizer company

EpiPen and EpiPen Jr are registered trademarks of Mylan Inc. licensed exclusively to its wholly-owned affiliate, Mylan Specialty L.P. of, Morgantown, WV 26505, U.S.A.®®

2014 by Meridian Medical Technologies, Inc.©

Revised: April 2014

EPIP-N:R00

EpiPen (Epinephrine) Auto-Injector 0.3 mg®

EpiPen Jr (Epinephrine) Auto-Injector 0.15 mg®

MyEpiPen.com

Register your EpiPen or EpiPen Jr Auto-Injector at and find out more about: MyEpiPen.com

- Free EpiPen Auto-Injector . It is important to keep your auto-injector up-to-date. Refill Reminder Program

Register up to 6 EpiPen or EpiPen Jr Auto- Injectors and receive automatic . Refill Reminder Alerts

- Receive periodic information related to allergies and allergens.
- Instructional Video

For more information about EpiPen or EpiPen Jr Auto-Injectors and proper use of the product, call Mylan at 1-877-446-3679 or visit . www.epipen.com

EpiPen Trainer Instructions for Use

In an emergency: Do not use the grey Trainer. Use your real yellow EpiPen or green EpiPen Jr Auto-Injector.®®

Important Information

- The Trainer label has a grey color.
- The Trainer contains no medicine and no needle.
- Periodically practice with the grey colored Trainer before an allergic emergency (anaphylaxis) happens to make sure you are able to safely use the real yellow EpiPen or green EpiPen Jr Auto-Injector in case of an emergency.
- Always carry your real yellow EpiPen or green EpiPen Jr Auto-Injector in case of an allergic emergency.

The EpiPen Trainer

Familiarize yourself with this grey Trainer. Practice until you are comfortable using it.

Your grey colored Trainer:

- Never put your thumb, other fingers, or hand over the Orange Tip.
- The Orange Tip is where the needle comes out of your EpiPen or EpiPen Jr Auto-Injector.

Practice Instructions

the Trainer for Simulated Injection 1 Prepare

- Grasp the grey Trainer in your fist with the orange tip pointing downward.
- With your other hand, without bending or twisting it. remove blue safety release by pulling straight up
- Removing the blue safety release unlocks the Trainer.

2 Administer the Trainer Simulation

- Hold the Trainer with the orange tip near the middle of the outer thigh (upper leg).
- until it ‘clicks.’ Keep the Trainer firmly pushed against the thigh at a 90º angle (perpendicular) to the thigh. Swing and firmly push the orange tip against the middle of the outer thigh

- Hold firmly against the thigh for approximately 10 seconds.
- and massage the injection area for 10 seconds. The orange tip automatically extends out after use. Remove the Trainer from the thigh

Note:
- In an actual emergency, you would need to seek medical help right away
- The actual auto-injector is made to work through clothing
- Do not inject into any other part of the body

3 To reset the Trainer

- Put the blue safety release back on the Trainer
- Place the orange tip on a hard surface
- Squeeze the sides of the orange tip and push down on the Trainer with the other hand

Note: With the real yellow EpiPen or green EpiPen Jr Auto-Injector, the orange tip covers the needle after self-injection to help protect you from accidentally sticking yourself or others.

Practice Session Information

In case of an allergic emergency, use the real yellow EpiPen or green EpiPen Jr Auto-Injector and not the grey Trainer.

Follow instructions above. Repeat as often as needed until you are able to self-inject quickly and correctly.

Reread:

- These Trainer Instructions for Use
- The “Patient Information” that comes with your EpiPen or EpiPen Jr Auto-Injector

Train others who could help you in an emergency:

- Your parents, caregivers, and others who may be in a position to administer EpiPen or EpiPen Jr should know how to help you during an allergic emergency (anaphylaxis). Before an emergency occurs, have them:
  - Practice activating the Trainer
  - Read these Trainer Instructions and the “Patient Information”

For more information about the EpiPen and EpiPen Jr Auto-Injector and the proper use of the products, go to www.epipen.com.

Caution:

Important differences between the Trainer and your real yellow EpiPen or green EpiPen Jr Auto-Injector

 | TRAINER (Grey) | EpiPen (Yellow) | EpiPen Jr (Green)
Contains medication? | NO | YES | YES
Has needle? | NO | YES | YES
Comes in Carrier Tube? | NO | YES | YES
Color of Label | Grey | Yellow | Green
Has expiration date? | NO | YES | YES
Can be reused? | YES | NO (use only once) | NO (use only once)
Okay to remove and replace safety release? | YES | NO (remove just once before use) | NO (remove just once before use)
Pressure needed to hold against thigh? | Moderate | Strong | Strong

This Trainer Instructions for Use has been approved by the U.S. Food and Drug Administration.

Manufactured for Mylan Specialty L.P., Morgantown, WV 26505, U.S.A. by Meridian Medical Technologies, Inc., Columbia, MD 21046, U.S.A., a Pfizer company

EpiPen and EpiPen Jr are registered trademarks of Mylan Inc. licensed exclusively to its wholly-owned affiliate, Mylan Specialty L. P. of Morgantown, WV 26505, U.S.A.®®

©2014 by Meridian Medical Technologies, Inc.
Revised: April 2014

EPIP-TN:R00